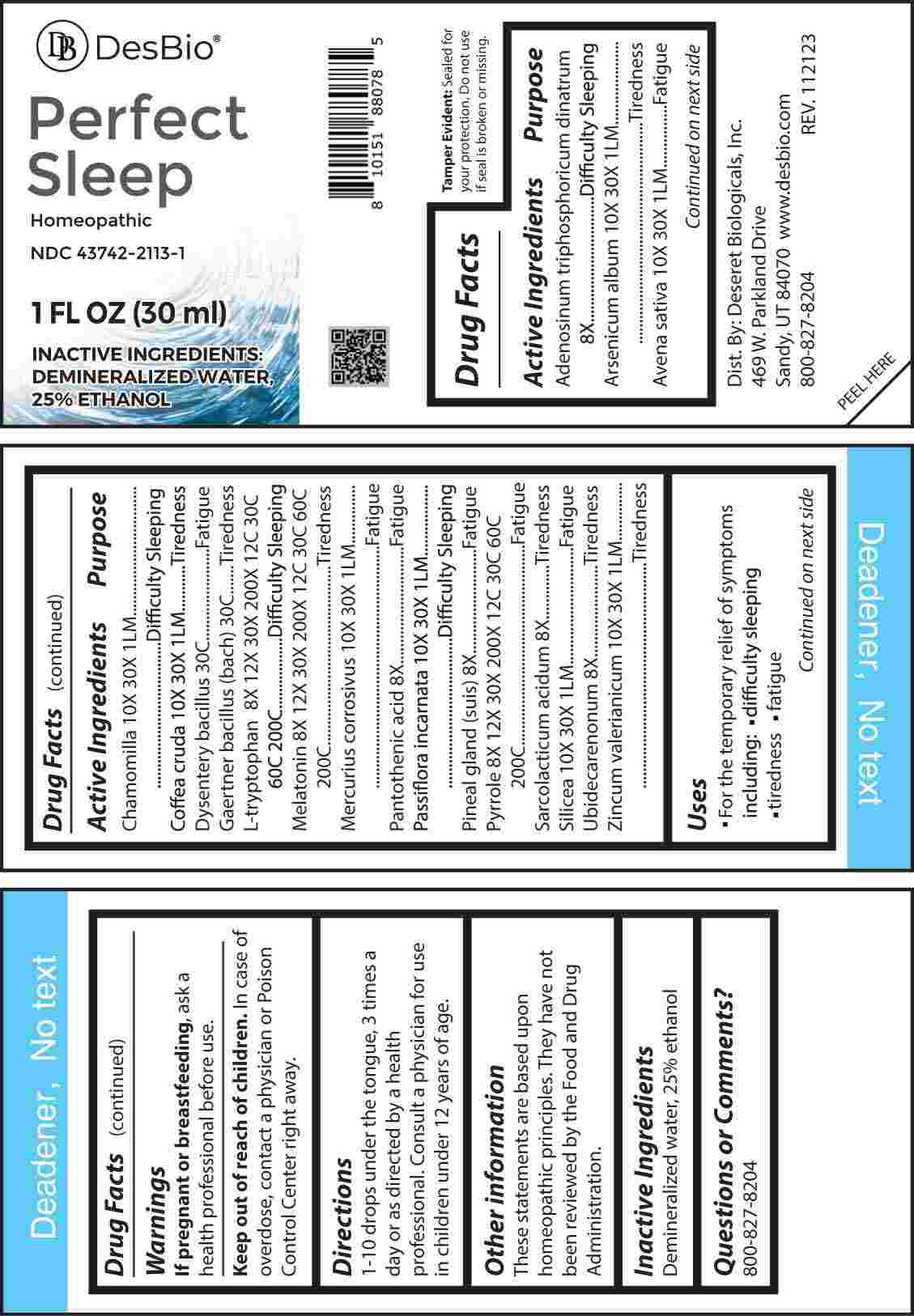 DRUG LABEL: Perfect Sleep
NDC: 43742-2113 | Form: LIQUID
Manufacturer: Deseret Biologicals, Inc.
Category: homeopathic | Type: HUMAN OTC DRUG LABEL
Date: 20240308

ACTIVE INGREDIENTS: ADENOSINE TRIPHOSPHATE DISODIUM 8 [hp_X]/1 mL; ARSENIC TRIOXIDE 10 [hp_X]/1 mL; AVENA SATIVA FLOWERING TOP 10 [hp_X]/1 mL; MATRICARIA CHAMOMILLA WHOLE 10 [hp_X]/1 mL; ARABICA COFFEE BEAN 10 [hp_X]/1 mL; SHIGELLA DYSENTERIAE 30 [hp_C]/1 mL; SALMONELLA ENTERICA ENTERICA SEROVAR ENTERITIDIS 30 [hp_C]/1 mL; TRYPTOPHAN 8 [hp_X]/1 mL; MELATONIN 8 [hp_X]/1 mL; MERCURIC CHLORIDE 10 [hp_X]/1 mL; PANTOTHENIC ACID 8 [hp_X]/1 mL; PASSIFLORA INCARNATA FLOWERING TOP 10 [hp_X]/1 mL; SUS SCROFA PINEAL GLAND 8 [hp_X]/1 mL; PYRROLE 8 [hp_X]/1 mL; LACTIC ACID, L- 8 [hp_X]/1 mL; SILICON DIOXIDE 10 [hp_X]/1 mL; UBIDECARENONE 8 [hp_X]/1 mL; ZINC VALERATE DIHYDRATE 10 [hp_X]/1 mL
INACTIVE INGREDIENTS: WATER; ALCOHOL

DRUG FACTS:

ACTIVE INGREDIENTS:

Adenosinum Triphosphoricum Dinatrum 8X, Arsenicum Album 10X, 30X, 1LM, Avena Sativa 10X, 30X, 1LM, Chamomilla 10X, 30X, 1LM, Coffea Cruda 10X, 30X, 1LM, Dysentery Bacillus 30C, Gaertner Bacillus (Bach) 30C, L-Tryptophan 8X, 12X, 30X, 200X, 12C, 30C, 60C, 200C, Melatonin 8X, 12X, 30X, 200X, 12C, 30C, 60C, 200C, Mercurius Corrosivus 10X, 30X, 1LM, Pantothenic Acid 8X, Passiflora Incarnata 10X, 30X, 1LM, Pineal Gland (Suis) 8X, Pyrrole 8X, 12X, 30X, 200X, 12C, 30C, 60C, 200C, Sarcolacticum Acidum 8X, Silicea 10X, 30X, 1LM, Ubidecarenonum 8X, Zincum Valerianicum 10X, 30X, 1LM.

PURPOSE

Adenosinum Triphosphoricum Dinatrum – Difficulty Sleeping, Arsenicum Album - Tiredness, Avena Sativa - Fatigue, Chamomilla – Difficulty Sleeping, Coffea Cruda - Tiredness, Dysentery Bacillus - Fatigue, Gaertner Bacillus (Bach) - Tiredness, L-Tryptophan – Difficulty Sleeping, Melatonin - Tiredness, Mercurius Corrosivus - Fatigue, Pantothenic Acid - Fatigue, Passiflora Incarnata – Difficulty Sleeping, Pineal Gland (Suis) - Fatigue, Pyrrole - Fatigue, Sarcolacticum Acidum - Tiredness, Silicea - Fatigue, Ubidecarenonum - Tiredness, Zincum Valerianicum - Tiredness

USES:

• For the temporary relief of the symptoms including:

• difficulty sleeping

• tiredness • fatigue

These statements are based upon homeopathic principles. They have not been reviewed by the Food and Drug Administration.

WARNINGS:

If pregnant or breast-feeding, ask a health professional before use.

Keep out of reach of children. In case of overdose, contact a physician or Poison Control Center right away.

Tamper Evident: Sealed for your protection. Do not use if seal is broken or missing.

KEEP OUT OF REACH OF CHILDREN:

In case of overdose, contact a physician or Poison Control Center right away.

DIRECTIONS:

1-10 drops under the tongue, 3 times a day or as directed by a health professional. Consult a physician for use in children under 12 years of age.

INACTIVE INGREDIENTS:

Demineralized water, 25% ethanol

QUESTIONS:

Dist. By: Deseret Biologicals, Inc.
469 W. Parkland Drive
Sandy, UT 84070

www.desbio.com

800-827-8204

PACKAGE LABEL DISPLAY:

DesBio

Perfect

Sleep

Homeopathic

NDC 43742-2113-1

1 FL OZ (30 ml)